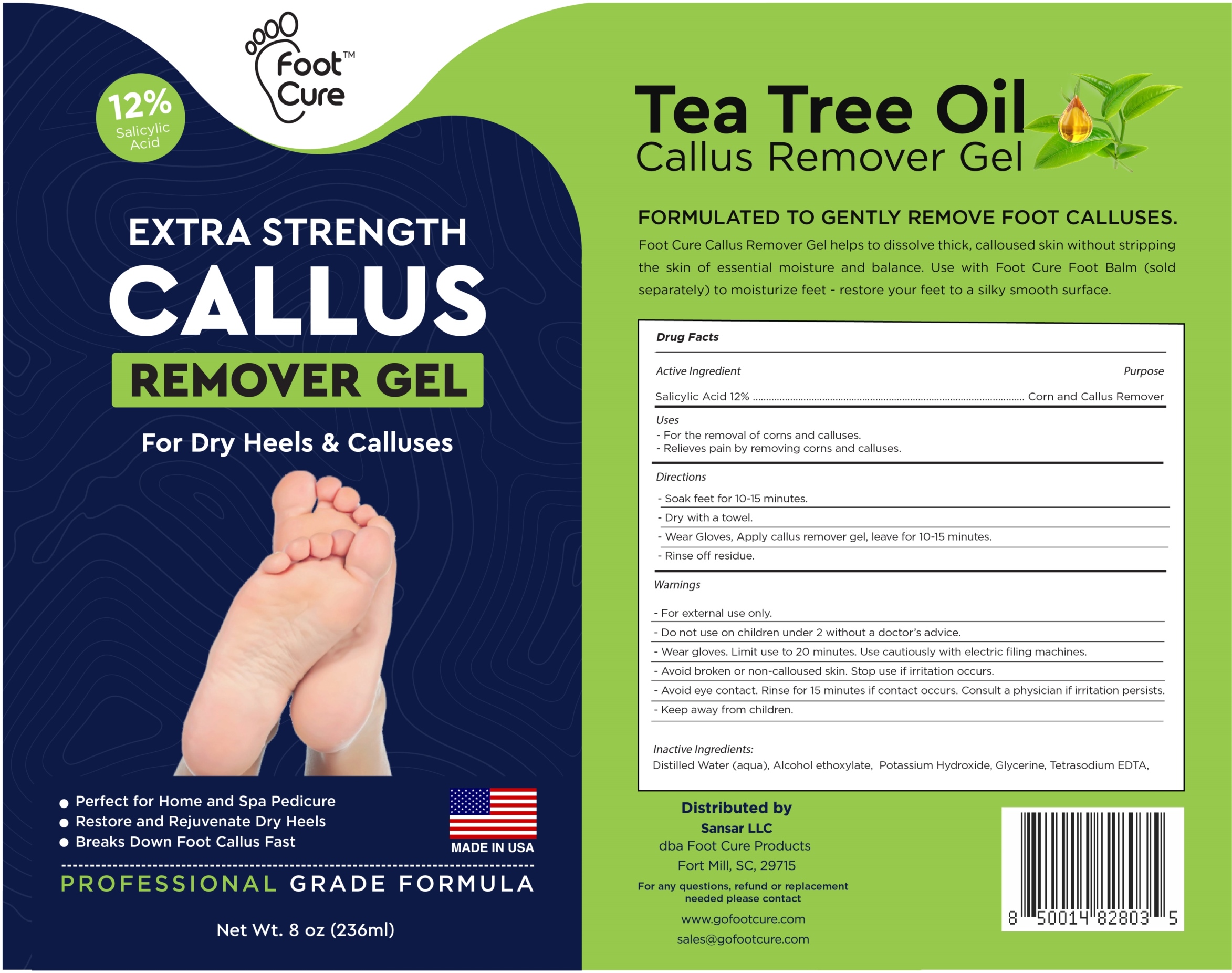 DRUG LABEL: Tea Tree Oil Callus Remover
NDC: 83691-007 | Form: GEL
Manufacturer: SANSAR, LLC
Category: otc | Type: HUMAN OTC DRUG LABEL
Date: 20250509

ACTIVE INGREDIENTS: SALICYLIC ACID 12 g/100 mL
INACTIVE INGREDIENTS: POTASSIUM HYDROXIDE; GLYCERIN; EDETATE SODIUM; 1-ETHOXYUNDECANE

Tea Tree Oil Callus Remover Gel

Active ingredient

Salicylic acid 12%

Purpose

Corn and callus remover

Uses

- for the removal of corns and calluses
- Relieves pain by removing corns and calluses

Warnings

For external use only.

Do not use on Children under 2 without a Doctor's advice.

When using this product

- Wear gloves. Limit use to 20 minutes. Use cautiously with electric filing machines.
- Avoid broken or non calloused skin.
- Avoid eye contact. Rinse for 15 minutes if contcat occurs. consult a physician if irritation persists.

KEEP OUT OF REACH OF CHILDREN

Keep out of the reach of children. If swallowed, get medical help or contact a Poison Control Center immediately.

Directions

- Soak feet for 10-15 minutes
- Dry with a towel
- Wear Gloves, apply callus remover gel, leave for 10-15 minutes.
- Rinse of residue.

Inactive Ingredients

Distilled water, Alcohol ethoxylate, Potassium Hydroxide, Glycerin, Tetrasodium EDTA